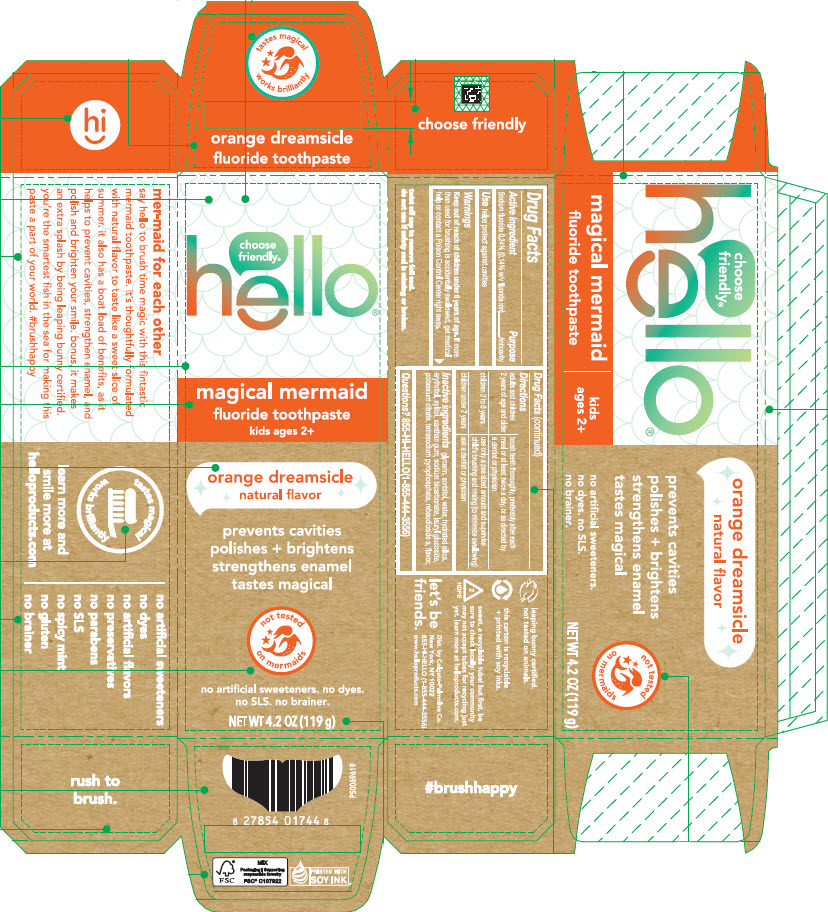 DRUG LABEL: Hello Magical Mermaid
NDC: 35000-680 | Form: GEL, DENTIFRICE
Manufacturer: Colgate-Palmolive Company
Category: otc | Type: HUMAN OTC DRUG LABEL
Date: 20250415

ACTIVE INGREDIENTS: SODIUM FLUORIDE 1.1 mg/1 g
INACTIVE INGREDIENTS: GLYCERIN; SORBITOL; WATER; HYDRATED SILICA; ERYTHRITOL; XYLITOL; XANTHAN GUM; SODIUM BICARBONATE; LAURYL GLUCOSIDE; POTASSIUM CITRATE; SODIUM PYROPHOSPHATE; REBAUDIOSIDE A

Hello® Magical Mermaid

Drug Facts

Active Ingredient

Sodium fluoride 0.24% (0.14% w/v fluoride ion)

Purpose

Anticavity

Use

helps protect against cavities

Warnings

Keep out of reach of children under 6 years of age.

If more than used for brushing is accidentally swallowed, get medical help or contact a Poison Control Center right away.

Directions

adults and children 2 years of age and older | brush teeth thoroughly, preferably after each meal or at least twice a day, or as directed by a dentist or physician
children 2 to 6 years | use only a pea sized amount and supervise child's brushing and rinsing (to minimize swallowing)
children under 2 years | ask a dentist or physician

Inactive ingredients

glycerin, sorbitol, water, hydrated silica, erythritol, xylitol, xanthan gum, sodium bicarbonate, lauryl glucoside, potassium citrate, tetrasodium pyrophosphate, rebaudioside a, flavor.

Questions?

855-HI-HELLO (1-855-444-3556)

Dist. by Colgate-Palmolive Co.
New York, NY 10022

PRINCIPAL DISPLAY PANEL - 119 g Tube Carton

choose
friendly®

hello®

magical mermaid

fluoride toothpaste
kids ages 2+

orange dreamsicle
natural flavor

prevents cavities
polishes + brightens
strengthens enamel
tastes magical

not tested
on mermaids

no artificial sweeteners. no dyes.
no SLS. no brainer.

NET WT 4.2 OZ (119 g)